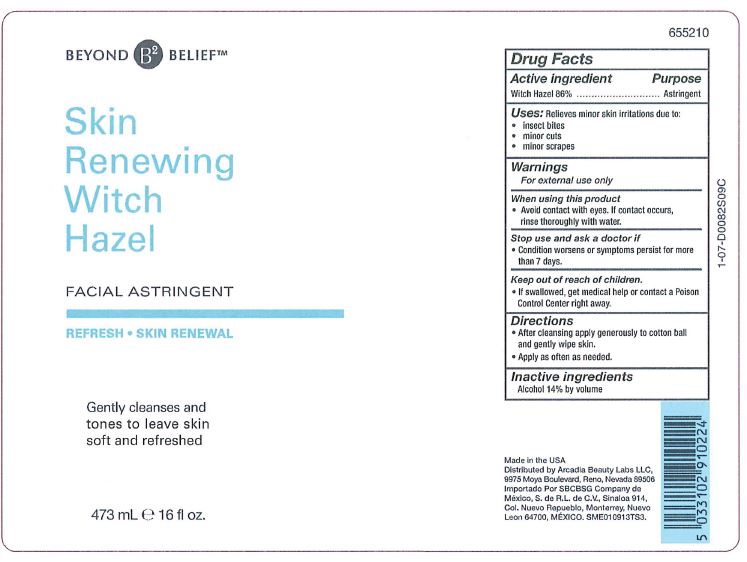 DRUG LABEL: Witch Hazel
NDC: 71990-001 | Form: LIQUID
Manufacturer: Arcadia Beauty Labs LLC
Category: otc | Type: HUMAN OTC DRUG LABEL
Date: 20241115

ACTIVE INGREDIENTS: WITCH HAZEL 86 g/100 mL
INACTIVE INGREDIENTS: ALCOHOL

Witch Hazel

Active Ingredient

Witch Hazel 86%

Purpose

Astringent

Uses: Relieves minor skin irritation due to:

- insect bites
- minor cuts
- minor scrapes

Warnings

For external use only

When using this product

- Avoid contact with eyes. If contact occurs, rinse thoroughly with water.

Stop use and ask a doctor if

- Condition worsens or symptoms persist for more than 7 days.

Keep out of reach of children.

- If swallowed, get medical help or contact a Poison Control Center right away.

Directions

- After cleansing apply generously to cotton ball and gently wipe skin.
- Apply as often as needed.

Inactive ingredients

Alcohol 14% by volume.

Principal Display Panel

BEYOND BELIEF

Skin Renewing Witch Hazel

FACIAL ASTRINGENT

REFRESH - SKIN RENEWAL

Gently cleanses and

tones to leave skin

soft and refreshed

473 mL 16 fl oz.